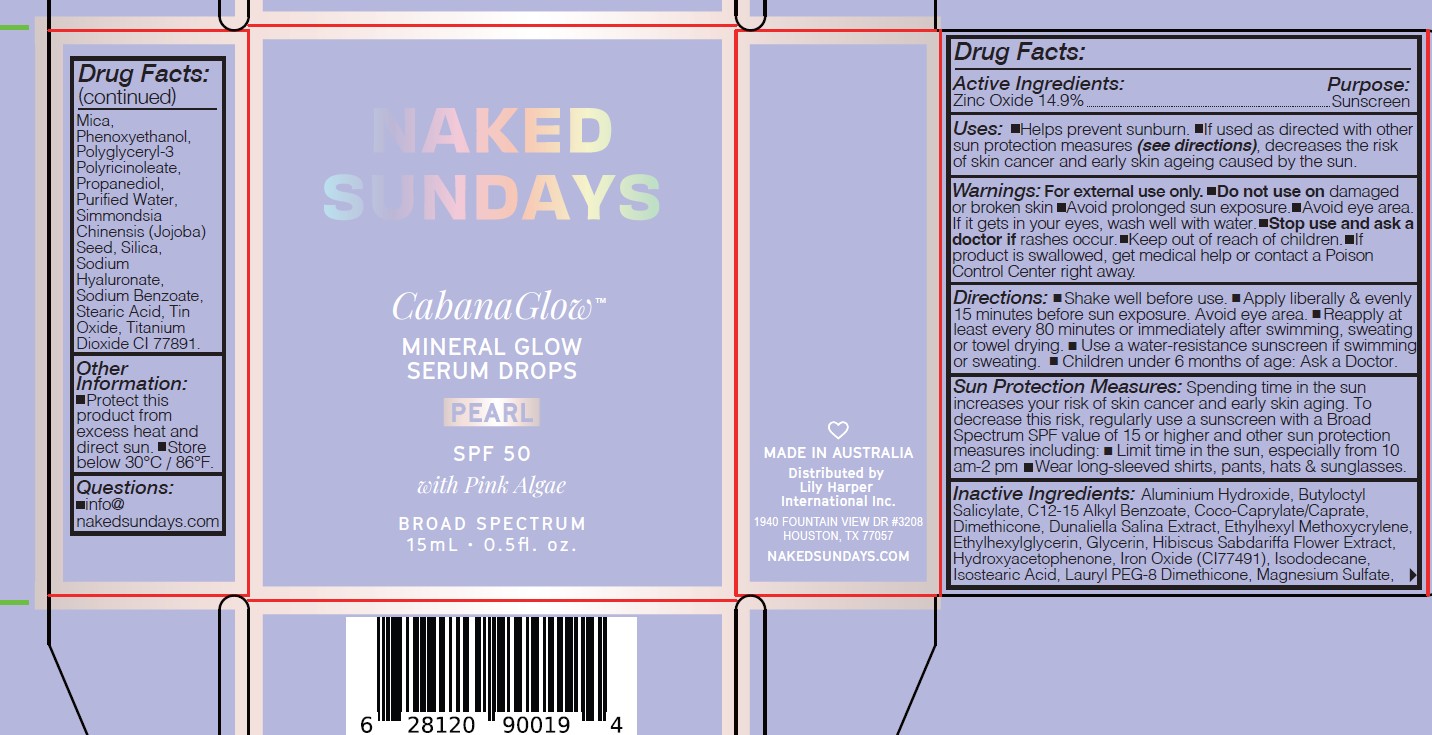 DRUG LABEL: NAKED SUNDAYS CABANA GLOW MINERAL GLOW SERUM DROPS PEARL 15mL with Pink Algae
NDC: 81104-256 | Form: LIQUID
Manufacturer: NAKED SUNDAYS PTY LTD
Category: otc | Type: HUMAN OTC DRUG LABEL
Date: 20250812

ACTIVE INGREDIENTS: ZINC OXIDE 14.9 g/100 mL
INACTIVE INGREDIENTS: GLYCERIN; CI 77891; SILICON DIOXIDE; SIMMONDSIA CHINENSIS SEED; DIMETHICONE; ETHYLHEXYLGLYCERIN; ALUMINUM HYDROXIDE; ETHYLHEXYL METHOXYCRYLENE; ALKYL (C12-15) BENZOATE; ISOSTEARIC ACID; STEARIC ACID; WATER; HYDROXYACETOPHENONE; PHENOXYETHANOL; PROPANEDIOL; HIBISCUS SABDARIFFA FLOWER; BUTYLOCTYL SALICYLATE; COCO-CAPRYLATE/CAPRATE; ISODODECANE; POLYGLYCERYL-3 PENTARICINOLEATE; LAURYL PEG-8 DIMETHICONE (300 CPS); MICA; MAGNESIUM SULFATE ANHYDROUS; DUNALIELLA SALINA; CI 77491; SODIUM BENZOATE; TIN OXIDE; SODIUM HYALURONATE

NAKED SUNDAYS CABANA GLOW MINERAL GLOW SERUM DROPS PEARL with Pink Algae

ACTIVE INGREDIENTS

Zinc Oxide 14.9%

Purpose

Sunscreen

USES

Uses: Helps prevent sunburn. If used as
directed with other sun protection measures
(see directions), decreases the risk of skin
cancer and early skin ageing caused by the sun.

WARNINGS

Warnings: For external use only. Do not use
on damaged or broken skin Avoid prolonged
sun exposure. If it gets in your eyes, wash well
with water. Keep out of reach of children.
Stop use and ask a doctor if rashes occur.
If product is swallowed, get medical help or
contact a Poison Control Center right away.

Keep out of reach of children. If product is swallowed, get medical help or contact a Poison Control Center right away.

DIRECTIONS

- SPRAY 7 TIMES WITH MOUTH AND LIPS CLOSED 8-10" AWAY FROM FACE 15 MINUTES BEFORE SUN EXPOSURE.
- Reapply after 80 minutes of swimming or sweating.
- Reapply immediately after towel drying.
- Reapply at least every 2 hours.
- Children under 3 years of age: Ask a doctor.

SUN PROTECTION MEASURES:

Spending time in the sun increases your risk of skin cancer and early skin aging. To decrease this risk, regularly use a sunscreen with a Broad Spectrum SPF value of 15 or higher and other sun protection measures including:

- Limit time in the sun, especially from 10.00AM - 2.00PM
- Wear long-sleeved shirts, pants, hats, and sunglasses

INACTIVE INGREDIENTS

Inactive Ingredients: Aluminum Hydroxide,
Aqua, Butyloctyl Salicylate, C12-15 Alkyl
Benzoate, Coco-Caprylate/Caprate, Dimethicone,
Dunaliella Salina Extract, Ethylhexyl
Methoxycrylene, Ethylhexylglycerin, Hibiscus
sabdariffa Flower Extract, Hydroxyacetophenone,
Iron Oxides, Isododecane, Isostearic Acid, Lauryl
PEG-8 Dimethicone, Magnesium Sulfate, Mica,
Phenoxyethanol, Polyglyceryl-2 Tetraisostearate,
Polyglyceryl-2 Tetraisostearate, Polyglyceryl-3
Polyricinoleate, Propanediol, Sodium Hyaluronate,
Stearic Acid, Silica, Simmondsia Chinensis
(Jojoba) Seed, Tin Oxide.

OTHER INFORMATION

Other Information: Protect this product
from excess heat and direct sun. Store below
30°C / 86°F.

USER SAFETY WARNINGS

Directions: Shake well before use.
Apply liberally and reapply every 80 minutes,
especially after swimming or towel drying.
Sun Protection Measures Spending time in
the sun increases your risk of skin cancer and
early skin aging. To decrease this risk, regularly
use a sunscreen with a Broad Spectrum SPF
value of 15 or higher and other sun protection
measures including: Limit lime in the sun,
especially from 10 am-2 pm Wear longsleeved
shirts, pants, hats, and sunglasses For
Children under 6 months of age ask a doctor